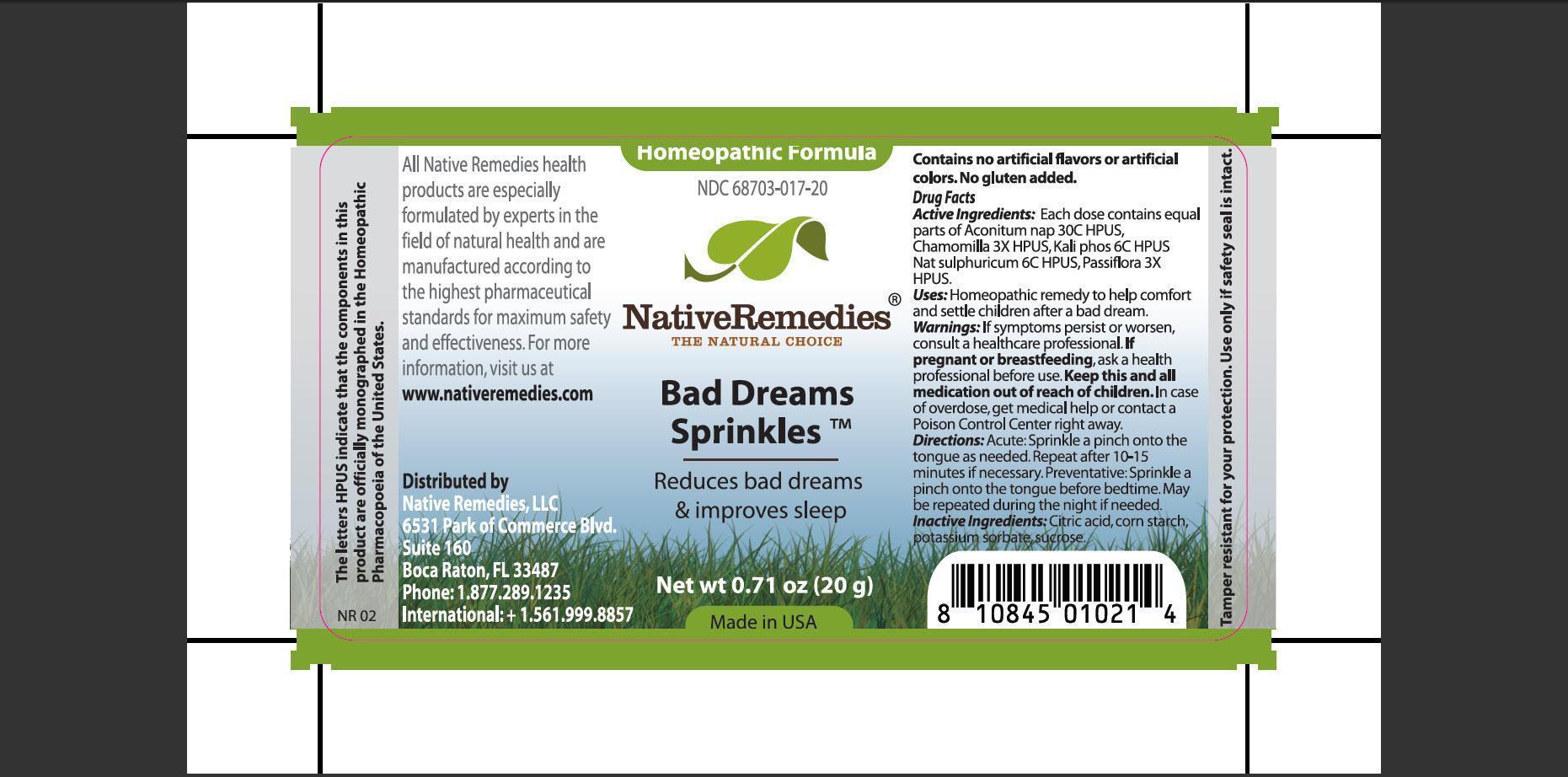 DRUG LABEL: Bad Dream Sprinkles
NDC: 68703-017 | Form: GRANULE
Manufacturer: Native Remedies, LLC
Category: homeopathic | Type: HUMAN OTC DRUG LABEL
Date: 20121024

ACTIVE INGREDIENTS: ACONITUM NAPELLUS 30 [hp_C]/40 mg; MATRICARIA RECUTITA 3 [hp_X]/40 mg; POTASSIUM PHOSPHATE, DIBASIC 6 [hp_C]/40 mg; SODIUM SULFATE 6 [hp_C]/40 mg; PASSIFLORA INCARNATA FLOWERING TOP 3 [hp_X]/40 mg
INACTIVE INGREDIENTS: CITRIC ACID MONOHYDRATE; STARCH, CORN; POTASSIUM SORBATE; SUCROSE

Bad Dream Sprinkles

PURPOSE

Reduces bad dreams and improves sleep.

ACTIVE INGREDIENT

Active Ingredients: Each dose contains equal parts of: Aconitum nap 30C HPUS, Chamomilla 3X HPUS, Kali phos 6C HPUS, Nat sulphuricum 6C HPUS, Passiflora 3X HPUS.

INDICATIONS AND USAGE

Uses: Homeopathic remedy to comfort and settle children after a bad dream.

WARNINGS

Warnings: If symptoms persist or worsen, consult a healthcare professional.

PREGNANCY OR BREAST FEEDING

If pregnant or breastfeeding, ask a health professional before use.

KEEP OUT OF REACH OF CHILDREN

Keep this and all medication out of reach of children.

OVERDOSAGE

In case of overdose, get medical help or contact a Poison Control Center right away.

DOSAGE AND ADMINISTRATION

Directions: Acute: Sprinkle a pinch onto the tongue as needed. Repeat after 10-15 minutes if necessary. Preventative: Sprinkle a pinch onto the tongue before bedtime. May be repeated during the night if needed.

INACTIVE INGREDIENT

Inactive Ingredients: Citric acid, corn starch, potassium sorbate, sucrose.

PATIENT COUNSELING INFORMATION

The letters HPUS indicate that the component(s) in this product is (are) officially monographed in the Homeopathic Pharmacopoeia of the United States.

All Native Remedies health products are especially formulated by experts in the field of natural health and are manufactured according to the highest pharmaceutical standards for maximum safety and effectiveness. For more information, visit us at www.nativeremedies.com

Distributed by
Native Remedies, LLC
6531 Park of Commerce Blvd. Suite 160
Boca Raton, FL 33487
Phone: +1.877.289.1235
International: +1.561.999.8857

Contains no artificial flavors or artificial colors. No gluten added.

STORAGE AND HANDLING

Tamper resistant for your protection. Use only if safety seal is intact.